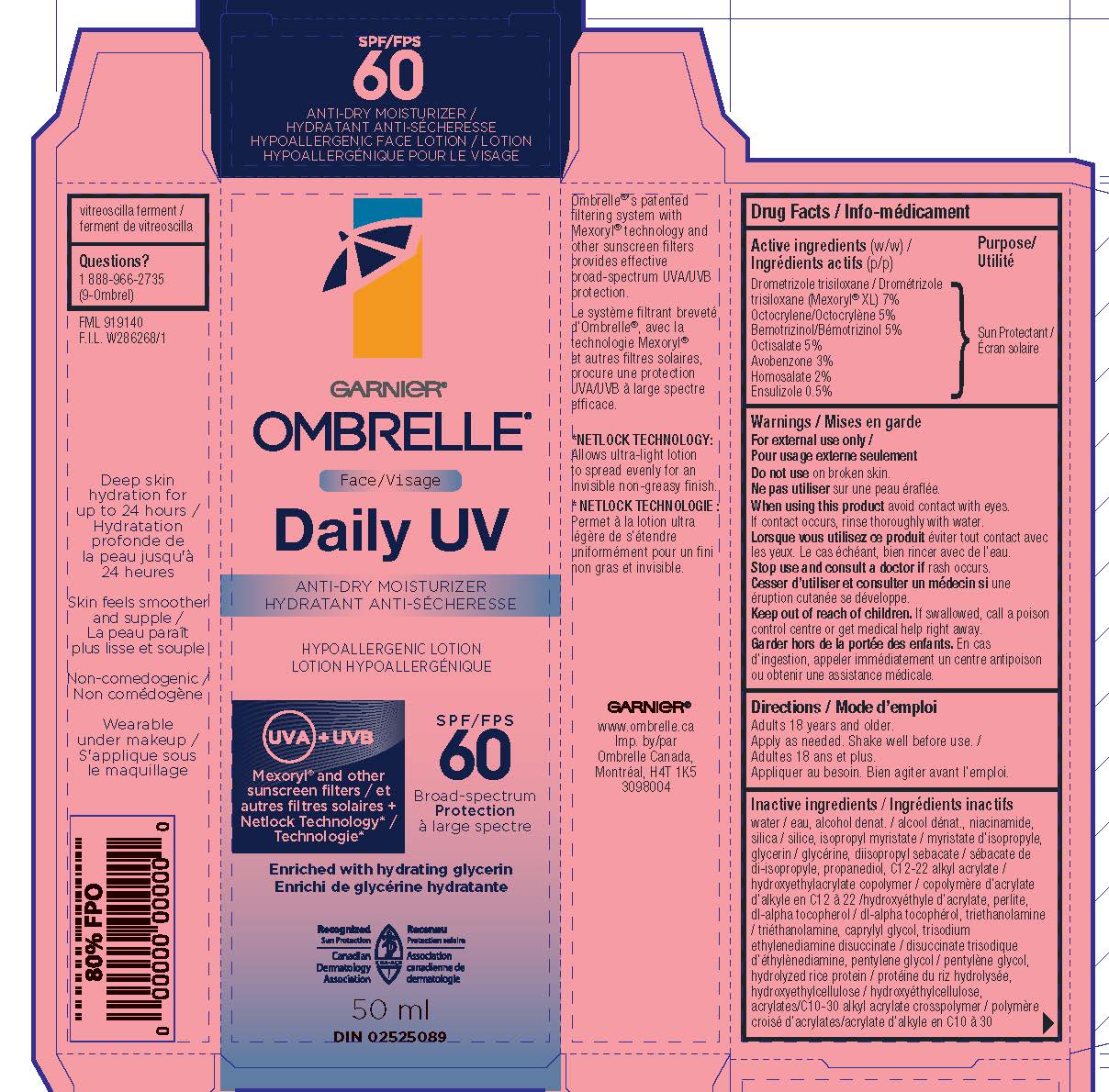 DRUG LABEL: Garnier Ombrelle Daily UV 60 Antidry Moisturizer Sunscreen
NDC: 49967-042 | Form: LOTION
Manufacturer: L'OREAL USA PRODUCTS INC
Category: otc | Type: HUMAN OTC DRUG LABEL
Date: 20260107

ACTIVE INGREDIENTS: AVOBENZONE 30 mg/1 mL; DROMETRIZOLE TRISILOXANE 70 mg/1 mL; HOMOSALATE 20 mg/1 mL; OCTISALATE 50 mg/1 mL; OCTOCRYLENE 50 mg/1 mL; BEMOTRIZINOL 50 mg/1 mL; ENSULIZOLE 5 mg/1 mL
INACTIVE INGREDIENTS: WATER; ALCOHOL; NIACINAMIDE; SILICON DIOXIDE; ISOPROPYL MYRISTATE; GLYCERIN; DIISOPROPYL SEBACATE; PROPANEDIOL; PERLITE; TOCOPHEROL; HYDROXYETHYL CELLULOSE, UNSPECIFIED; TROLAMINE; TRISODIUM ETHYLENEDIAMINE DISUCCINATE; PENTYLENE GLYCOL; CAPRYLYL GLYCOL; VITREOSCILLA LYSATE

Drug Facts

Active ingredients

DROMETRIZOLE TRISILOXANE 7%
OCTOCRYLENE 5%
BEMOTRIZINOL 5%
OCTISALATE 5%
AVOBENZONE 3%
HOMOSALATE 2%
ENSULIZOLE 0.50%

Warnings

For external use only. Do not use on broken skin. When using this product avoid contact witheyes. If contact occurs, rinse thoroughlly with water. Stop use and ask a doctor if rash occurs. Keep out of reach of children. If swallowed get medical help or contact a poison control center right away.

Directions

Adults 18 years and older. Apply as needed. Shake well before use.

Inactive ingredients

water, alcohol denat., niacinamide, silica, isopropyl myristate, glycerin, diisopropyl sebacate, propanediol, c12-22 alkyl acrylate/hydroxyethylacrylate copolymer, perlite, tocopherol, hydrolyzed rice protein, hydroxyethylcellulose, triethanolamine, trisodium ethylenediamine disuccinate, pentylene glycol, caprylyl glycol, acrylates/c10-30 alkyl acrylate crosspolymer, vitreoscilla ferment